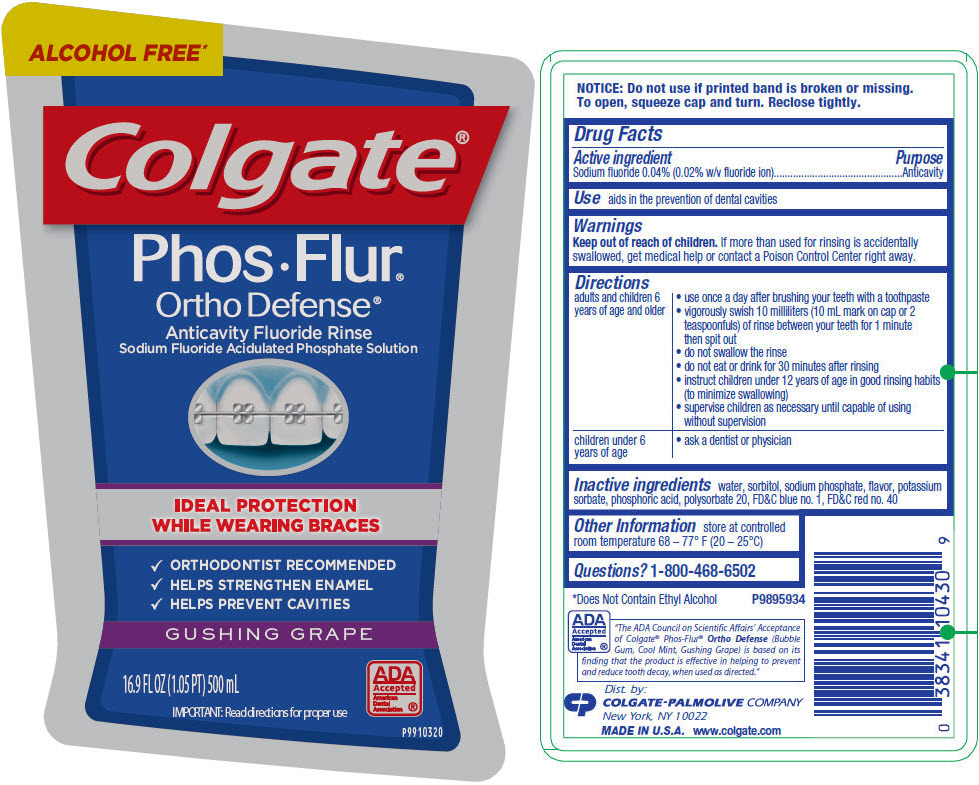 DRUG LABEL: Colgate Phos-Flur Ortho Defense Alcohol Free Anticavity Gushing Grape Fluoride
NDC: 0126-0034 | Form: RINSE
Manufacturer: Colgate Oral Pharmaceuticals, Inc.
Category: otc | Type: HUMAN OTC DRUG LABEL
Date: 20240112

ACTIVE INGREDIENTS: SODIUM FLUORIDE 2 mg/10 mL
INACTIVE INGREDIENTS: WATER; SORBITOL; SODIUM PHOSPHATE; POTASSIUM SORBATE; PHOSPHORIC ACID; POLYSORBATE 20; FD&C BLUE NO. 1; FD&C RED NO. 40

Colgate® Phos-Flur® Ortho Defense® Alcohol Free Anticavity Gushing Grape Fluoride Rinse

Drug Facts

Active ingredient

Sodium fluoride 0.04% (0.02% w/v fluoride ion)

Purpose

Anticavity

Use

aids in the prevention of dental cavities

Warnings

Keep out of reach of children. If more than used for rinsing is accidentally swallowed, get medical help or contact a Poison Control Center right away.

Directions

adults and children 6 years of age and older | - use once a day after brushing your teeth with a toothpaste - vigorously swish 10 milliliters (10 mL mark on cap or 2 teaspoonfuls) of rinse between your teeth for 1 minute then spit out - do not swallow the rinse - do not eat or drink for 30 minutes after rinsing - instruct children under 12 years of age in good rinsing habits (to minimize swallowing) - supervise children as necessary until capable of using without supervision
children under 6 years of age | - ask a dentist or physician

Inactive ingredients

water, sorbitol, sodium phosphate, flavor, potassium sorbate, phosphoric acid, polysorbate 20, FD&C blue no. 1, FD&C red no. 40

Other Information

store at controlled room temperature 68 – 77° F (20 – 25°C)

Questions?

1-800-468-6502

Dist. by:
COLGATE-PALMOLIVE COMPANY
New York, NY 10022

PRINCIPAL DISPLAY PANEL - 500 mL Bottle Label

ALCOHOL FREE*

Colgate®

Phos•Flur®

Ortho Defense®

Anticavity Fluoride Rinse
Sodium Fluoride Acidulated Phosphate Solution

IDEAL PROTECTION
WHILE WEARING BRACES

✓ ORTHODONTIST RECOMMENDED
✓ HELPS STRENGTHEN ENAMEL
✓ HELPS PREVENT CAVITIES

GUSHING GRAPE

16.9 FL OZ (1.05 PT) 500 mL

IMPORTANT: Read directions for proper use

ADA
Accepted
American
Dental
Association ®

P9910320